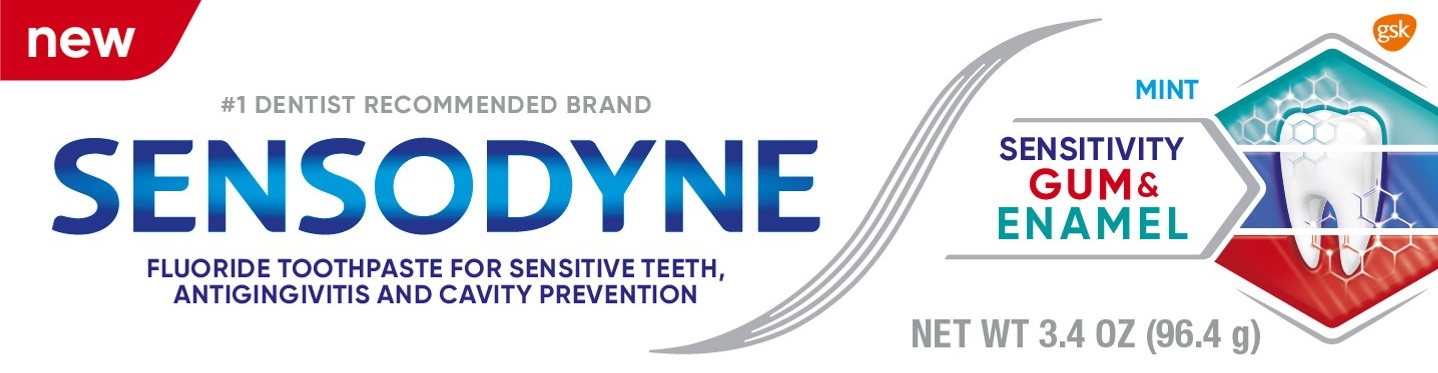 DRUG LABEL: SENSODYNE

NDC: 0135-5022 | Form: PASTE
Manufacturer: Haleon US Holdings LLC
Category: otc | Type: HUMAN OTC DRUG LABEL
Date: 20240307

ACTIVE INGREDIENTS: STANNOUS FLUORIDE 1.1 mg/1 g
INACTIVE INGREDIENTS: GLYCERIN; POLYETHYLENE GLYCOL 400; HYDRATED SILICA; SODIUM TRIPOLYPHOSPHATE, UNSPECIFIED FORM; SODIUM LAURYL SULFATE; TITANIUM DIOXIDE; COCAMIDOPROPYL BETAINE; SACCHARIN SODIUM

Drug Facts

Active ingredient

Stannous fluoride 0.454% (0.15% w/v fluoride ion)

Purposes

Anticavity, Antigingivitis, Antihypersensitivity

Uses

- aids in the prevention of dental cavities.
- helps control bleeding gums.
- helps interfere with harmful effects of plaque associated with gingivitis.
- builds increasing protection against painful sensitivity of the teeth to cold, heat, acids, sweets, or contact.

Warnings

Stop use and ask a dentist if

- the problem persists or worsens. Sensitive teeth may indicate a serious problem that may need prompt care by a dentist.
- pain/sensitivity still persists after 4 weeks of use.
- gingivitis, bleeding, or redness persists for more than 2 weeks.
- you have painful or swollen gums, pus from the gum line, loose teeth, or increasing spacing between the teeth. These maybe signs or symptoms of periodontitis, a serious form of gum disease.

Keep out of reach of children.

If more than used for brushing is accidentally swallowed, get medical help or contact a Poison Control Center right away.

Directions

- adults and children 12 years of age and older:
  - apply at least a 1-inch strip of the product onto a soft bristle toothbrush.
  - brush teeth thoroughly for at least 1 minute twice a day (morning and evening), and not more than 3 times a day, or as recommended by a dentist or doctor. Make sure to brush all sensitive areas of the teeth. Minimize swallowing. Spit out after brushing.
- children under 12 years of age:Consult a dentist or doctor.

Other information

- products containing stannous fluoride may produce surface staining of the teeth. Adequate toothbrushing may prevent these stains which are not harmful or permanent and may be removed by your dentist.
- this product is specially formulated to help prevent staining.
- do not store above 25°C (77°F)

Inactive ingredients

glycerin, PEG-8, hydrated silica, pentasodium triphosphate, flavor, sodium lauryl sulfate, titanium dioxide, polyacrylic acid, cocamidopropyl betaine, sodium saccharin, silica

Questions or comments?

1-866-844-2797

Additional Information

ALWAYS FOLLOW THE LABEL

SENSODYNE

SENSITIVITY
GUM &
ENAMEL

Gum recession and enamel wear are the two leading causes of sensitive teeth. Gum problems are caused by a build-up of plaque bacteria along the gum line. Enamel wear can be caused by acids in

everyday foods and drinks.

Sensodyne Sensitivity, Gum & Enamelis a daily toothpaste with a clinically proven ingredient to relieve sensitive teeth and improve gum health, while also strengthening the enamel.

1. Builds a protective layer over the sensitive areas
2. Formula with stannous fluoride targets & removes plaque bacteria** in between teeth & gumline.
3. Strengthens enamel surface and protects teeth from acids, while being gentle on enamel.

*with twice daily brushing.
**plaque bacteria associated with gingivitis to help reduce swollen, bleeding gums.

Trademarks owned or licensed by GSK. @2022 GSK or licensor.

Distributed by: GSK Consumer Healthcare
Warren, NJ 07059. Made in Germany

CARTON
RECYCLE

Principal Display Panel

new

#1 Dentist RecommendED Brand

SENSODYNE

MINT
SENSITIVITY GUM & ENAMEL

FLUORIDE TOOTHPASTE FOR SENSITIVE TEETH,
ANTI-GINGIVITIS AND CAVITY PREVENTION

NEW WT 3.4 OZ (96.4 g)

20041 Front Carton